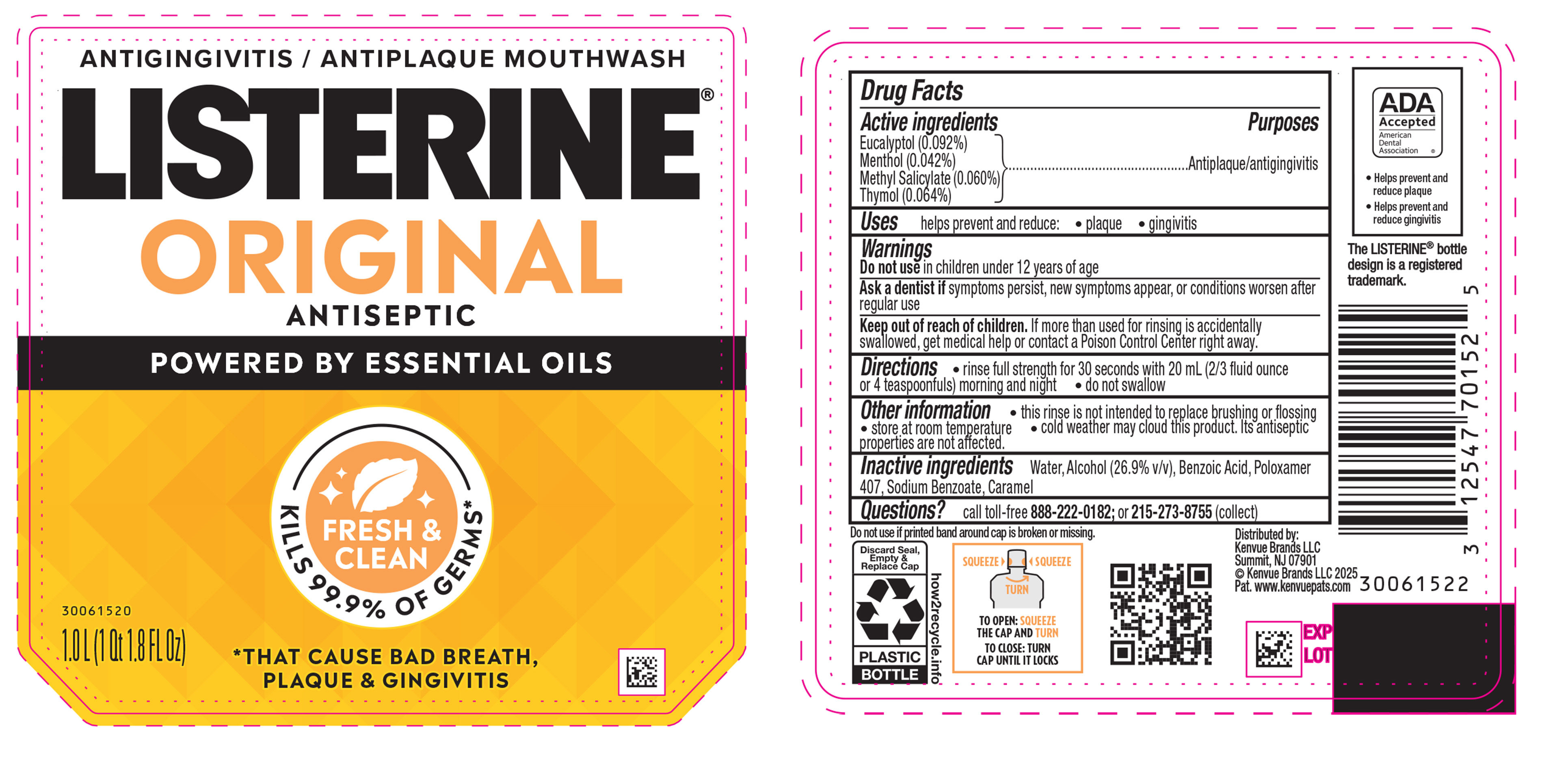 DRUG LABEL: Listerine Original Intense Antiseptic Antigingivitis/ Antiplaque Mouthwash
NDC: 69968-0955 | Form: MOUTHWASH
Manufacturer: Kenvue Brands LLC
Category: otc | Type: HUMAN OTC DRUG LABEL
Date: 20251210

ACTIVE INGREDIENTS: METHYL SALICYLATE 0.6 mg/1 mL; THYMOL 0.64 mg/1 mL; EUCALYPTOL 0.92 mg/1 mL; MENTHOL 0.42 mg/1 mL
INACTIVE INGREDIENTS: WATER; ALCOHOL; POLOXAMER 407; BENZOIC ACID; SODIUM BENZOATE; CARAMEL

Listerine Original Intense Antiseptic Antigingivitis/ Antiplaque Mouthwash

Drug Facts

Active ingredient

Eucalyptol (0.092%)

Menthol (0.042%)

Methyl Salicylate (0.060%)

Thymol (0.064%)

Purpose

Antiplaque/antigingivitis

Uses

helps prevent and reduce: • plaque • gingivitis

Warnings

Do not use in children under 12 years of age

Ask a dentist if symptoms persist, new symptoms appear, or conditions worsen after regular use

Keep out of reach of children. If more than used for rinsing is accidentally swallowed, get medical help or contact a Poison Control Center right away.

Directions

• rinse full strength for 30 seconds with 20 mL (2/3 fluid ounce or 4 teaspoonfuls) morning and night

• do not swallow

Other information

- this rinse is not intended to replace brushing or flossing
- store at room temperature
- cold weather may cloud this product. Its antiseptic properties are not affected.

Inactive ingredients

Water, Alcohol (26.9% v/v), Benzoic Acid, Poloxamer 407, Sodium Benzoate, Caramel

Questions?

call toll-free 888-222-0182; or 215-273-8755 (collect)

Distributed by:
Kenvue Brands LLC
Summit, NJ 07901

PRINCIPAL DISPLAY PANEL - 1 L Bottle Label

ANTIGINGIVITIS / ANTIPLAQUE MOUTHWASH

LISTERINE®

ORIGINAL

ANTISEPTIC

POWERED BY ESSENTIAL OILS

FRESH &

CLEAN

KILLS 99.9% OF GERMS*

*THAT CAUSE BAD BREATH,

PLAQUE & GINGIVITIS

1.0 L (1 Qt 1.8FL Oz)